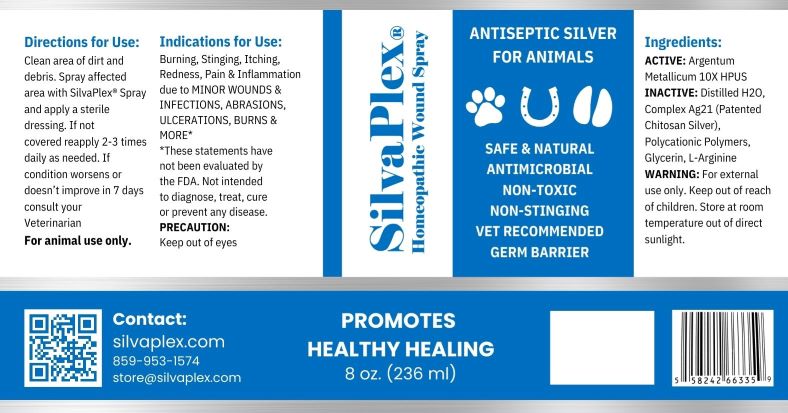 DRUG LABEL: SilvaPlex Wound
NDC: 72363-015 | Form: SPRAY
Manufacturer: AG Essence
Category: homeopathic | Type: HUMAN OTC DRUG LABEL
Date: 20250109

ACTIVE INGREDIENTS: SILVER 0.047 g/236 g
INACTIVE INGREDIENTS: WATER 231.468 g/236 g; GLYCERIN 2.37 g/236 g; CHITOSAN LOW MOLECULAR WEIGHT (20-200 MPA.S) 0.937 g/236 g; ARGININE 0.944 g/236 g; ANHYDROUS CITRIC ACID 0.234 g/236 g

DIRECTIONS FOR USE

Clean area of dirt and debris. Spray affected area with SilvaPlex Spray and apply a sterile dressing. If not covered reapply 2-3 times daily as neede. If condition worsens or doesn't improve in 7 days consult your Veterinarian.

WARNING

For external use only.

Precaution:

Keep out of eyes.

Ingredients

Active: Argentum Metallicum 10X HPUS

Ingredients

Inactive: Distilled Water, Complex Ag21, Polycationic Polymers, Glycerin, L-Arginine

Indications for Use

Burning, Stinging, Itching, Redness, Pain & Inflammation due to MINOR WOUNDS & INFECTIONS, ABRASIONS, ULCERATIONS, BURNS & MORE

WARNING:

Keep out of reach of children

SilvaPlex Wound Spray